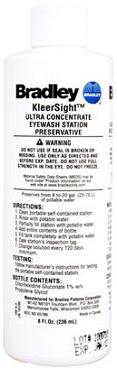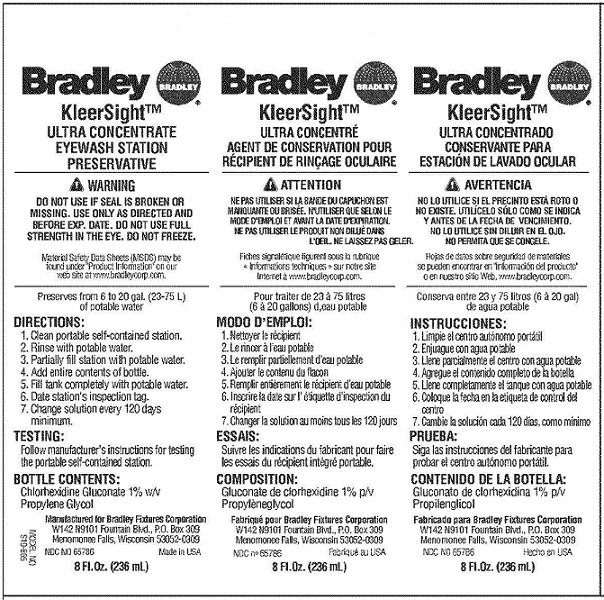 DRUG LABEL: KleerSight
NDC: 65786-1717 | Form: CONCENTRATE
Manufacturer: Bradley Fixtures Corporation
Category: otc | Type: HUMAN OTC DRUG LABEL
Date: 20100311

ACTIVE INGREDIENTS: Chlorhexidine Gluconate 2.36 mL/236 mL

Bradley KleerSight Ultra Concentrate

WARNINGS

WARNING: DO NOT USE IF SEAL IS BROKEN OR MISSING. USE ONLY AS DIRECTED AND BEFORE EXP. DATE. DO NOT USE FULL STRENGTH IN THE EYE. DO NOT FREEZE.

DIRECTIONS:

1. Clean portable self-contained station.
2. Rinse with portable water.
3. Partially fill station with portable water.
4. Add entire contents of bottle.
5. Fill tank completely with portable water.
6. Date station's inspection tag.
7. Change solution every 120 days or less as required.

TESTING:

Follow manufacturer's instructions for testing the portable self-contained station.

PACKAGE LABEL

REPRESENTATIVE PACKAGING

Bradley KleerSightTM ULTRA CONCENTRATE EYE WASH STATION PRESERVATIVE

WARNING: DO NOT USE IF SEAL IS BROKEN OR MISSING. USE ONLY AS DIRECTED AND BEFORE EXP. DATE. DO NOT USE FULL STRENGTH IN THE EYE. DO NOT FREEZE.

Material Safety Data Sheets (MSDS) may be found under 'Product Information' on our website at www.bradleycorp.com.

Preserves from 6 to 20 gal. (23-75 L) of portable water.

DIRECTIONS:

1. Clean portable self-contained station.
2. Rinse with portable water.
3. Partially fill station with portable water.
4. Add entire contents of bottle.
5. Fill tank completely with portable water.
6. Date station's inspection tag.
7. Change solution every 120 days minimum.

TESTING:

Follow manufacturer's instructions for testing the portable self-contained station.

BOTTLE CONTENTS:

Chlorhexidine Gluconate 1% w/v
Propylene Glycol

Manufactured for Bradley Fixtures Corporation
W142 N9101 Fountain Blvd. P.O. Box 309
Menomonee Falls, Wisconsin 53052-0309

NDC NO 65786

8 Fl. Oz. (236 mL)

Made in USA

MODEL NO S19-865

8 Ounce bottle of KleerSightTM Concentrate